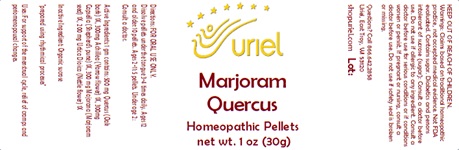 DRUG LABEL: Marjoram Quercus
NDC: 48951-7020 | Form: PELLET
Manufacturer: Uriel Pharmacy Inc.
Category: homeopathic | Type: HUMAN OTC DRUG LABEL
Date: 20240221

ACTIVE INGREDIENTS: SWEET MARJORAM 1 [hp_X]/1 1; CAPSELLA BURSA-PASTORIS 1 [hp_X]/1 1; URTICA DIOICA LEAF 1 [hp_X]/1 1; QUERCUS ROBUR WHOLE 1 [hp_X]/1 1; ACHILLEA MILLEFOLIUM 1 [hp_X]/1 1
INACTIVE INGREDIENTS: SUCROSE

Marjoram Quercus

INDICATIONS AND USAGE

Directions: FOR ORAL USE ONLY.

DOSAGE AND ADMINISTRATION

Dissolve pellets under the tongue 3-4 times daily. Ages 12 and older: 10 pellets. Ages 2-11: 5 pellets. Under age 2: Consult a doctor.

ACTIVE INGREDIENT

Active Ingredients: 1 gm contains: 500 mg Quercus (Oak bark) 1X, 300mg Achillea (Yarrow flower) 1X, 300mg Capsella (Shepherd's purse) 1X, 300 mg Majorana (Marjoram seed) 1X, 200 mg Urtica Dioica (Nettle flower) 1X

Inactive Ingredient: Organic sucrose

"prepared using rhythmical processes"

PURPOSE

Uses: For support of the menstrual cycle, relief of cramps and periomenopausal changes.

KEEP OUT OF REACH OF CHILDREN.

WARNINGS

Warnings: Claims based on traditional homeopathic practice, not accepted medical evidence. Not FDA evaluated. Contains sugar. Diabetics and persons intolerant of sucrose (sugar): Consult a doctor before use. Do not use if allergic to any ingredient. Consult a doctor before use for serious conditions or if conditions worsen or persist. If pregnant or nursing, consult a doctor before use. Do not use if safety seal is broken or missing.

Questions? Call 866.642.2858
Uriel, East Troy WI 53120
shopuriel.com Lot: